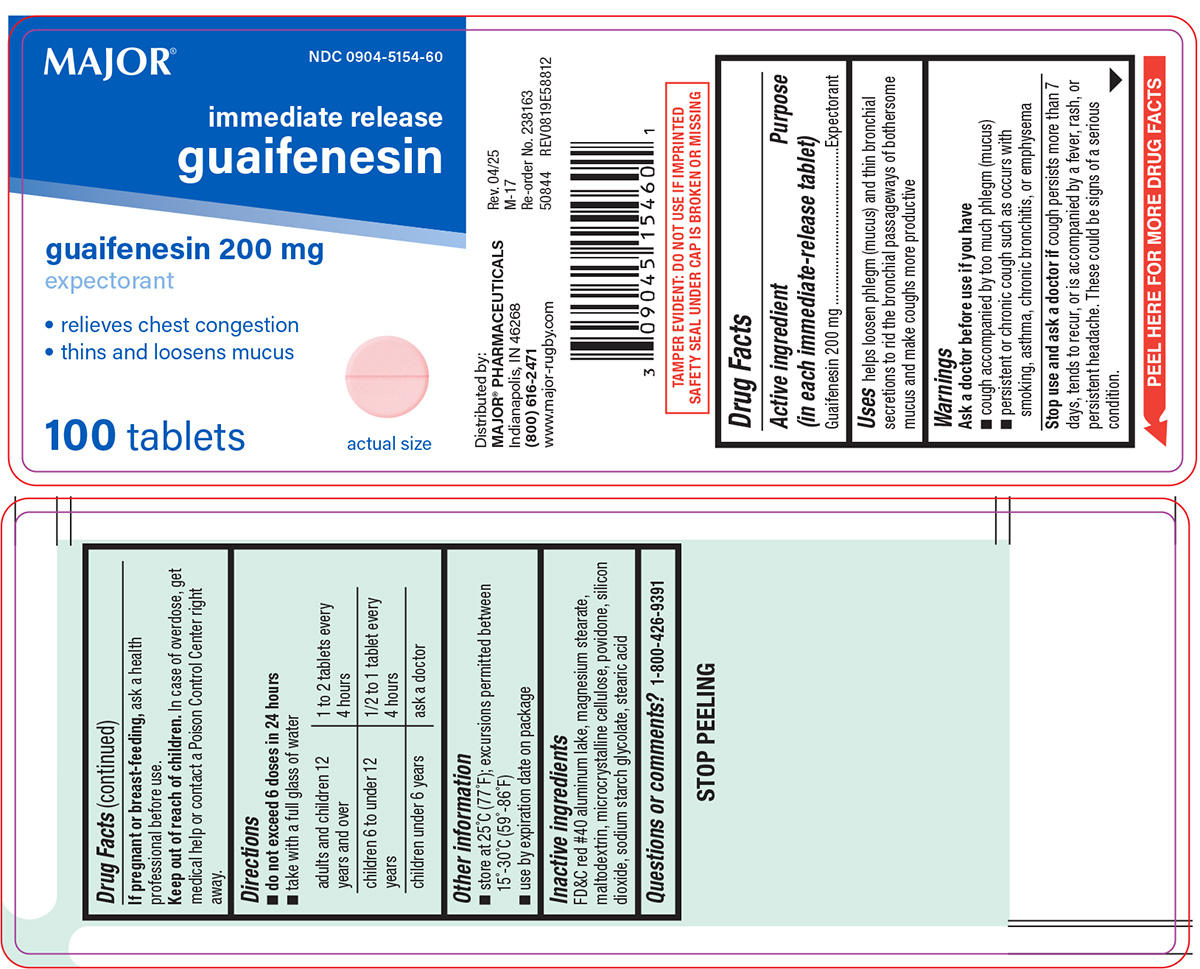 DRUG LABEL: Guaifenesin
NDC: 0904-5154 | Form: TABLET
Manufacturer: Major Pharmaceuticals
Category: otc | Type: HUMAN OTC DRUG LABEL
Date: 20250602

ACTIVE INGREDIENTS: GUAIFENESIN 200 mg/1 1
INACTIVE INGREDIENTS: FD&C RED NO. 40 ALUMINUM LAKE; MAGNESIUM STEARATE; MALTODEXTRIN; MICROCRYSTALLINE CELLULOSE; POVIDONE, UNSPECIFIED; SILICON DIOXIDE; SODIUM STARCH GLYCOLATE TYPE A POTATO; STEARIC ACID

Major 44-588

Active ingredient (in each immediate-release tablet)

Guaifenesin 200 mg

Purpose

Expectorant

Uses

helps loosen phlegm (mucus) and thin bronchial secretions to rid the bronchial passageways of bothersome mucus and make coughs more productive

Warnings

Ask a doctor before use if you have

- cough accompanied by too much phlegm (mucus)
- persistent or chronic cough such as occurs with smoking, asthma, chronic bronchitis, or emphysema

Stop use and ask a doctor if

cough persists more than 7 days, tends to recur, or is accompanied by a fever, rash, or persistent headache. These could be signs of a serious condition.

If pregnant or breast-feeding,

ask a health professional before use.

Keep out of reach of children.

In case of overdose, get medical help or contact a Poison Control Center right away.

Directions

- do not exceed 6 doses in 24 hours
- take with a full glass of water

adults and children 12 years and over | 1 to 2 tablets every 4 hours
children 6 to under 12 years | ½ to 1 tablet every 4 hours
children under 6 years | ask a doctor

Other information

- store at 25ºC (77ºF); excursions permitted between 15º-30ºC (59º-86ºF)
- use by expiration date on package

Inactive ingredients

FD&C red #40 aluminum lake, magnesium stearate, maltodextrin, microcrystalline cellulose, povidone, silicon dioxide, sodium starch glycolate, stearic acid

Questions or comments?

1-800-426-9391

Principal Display Panel

MAJOR® NDC 0904-5154-60

Immediate Release
Guaifenesin

guaifenesin 200 mg
Expectorant

•Relieves Chest Congestion
•Thins and Loosens Mucus

Actual Size

100 Tablets

TAMPER EVIDENT: DO NOT USE IF IMPRINTED
SAFETY SEAL UNDER CAP IS BROKEN OR MISSING

Distributed by: MAJOR® PHARMACEUTICALS
Indianapolis, IN 46268 (800) 616-2471
www.major-rugby.com
Rev. 04/25 M-17 Re-order No. 238163

50844 REV0819E58812

MAJOR 44-588